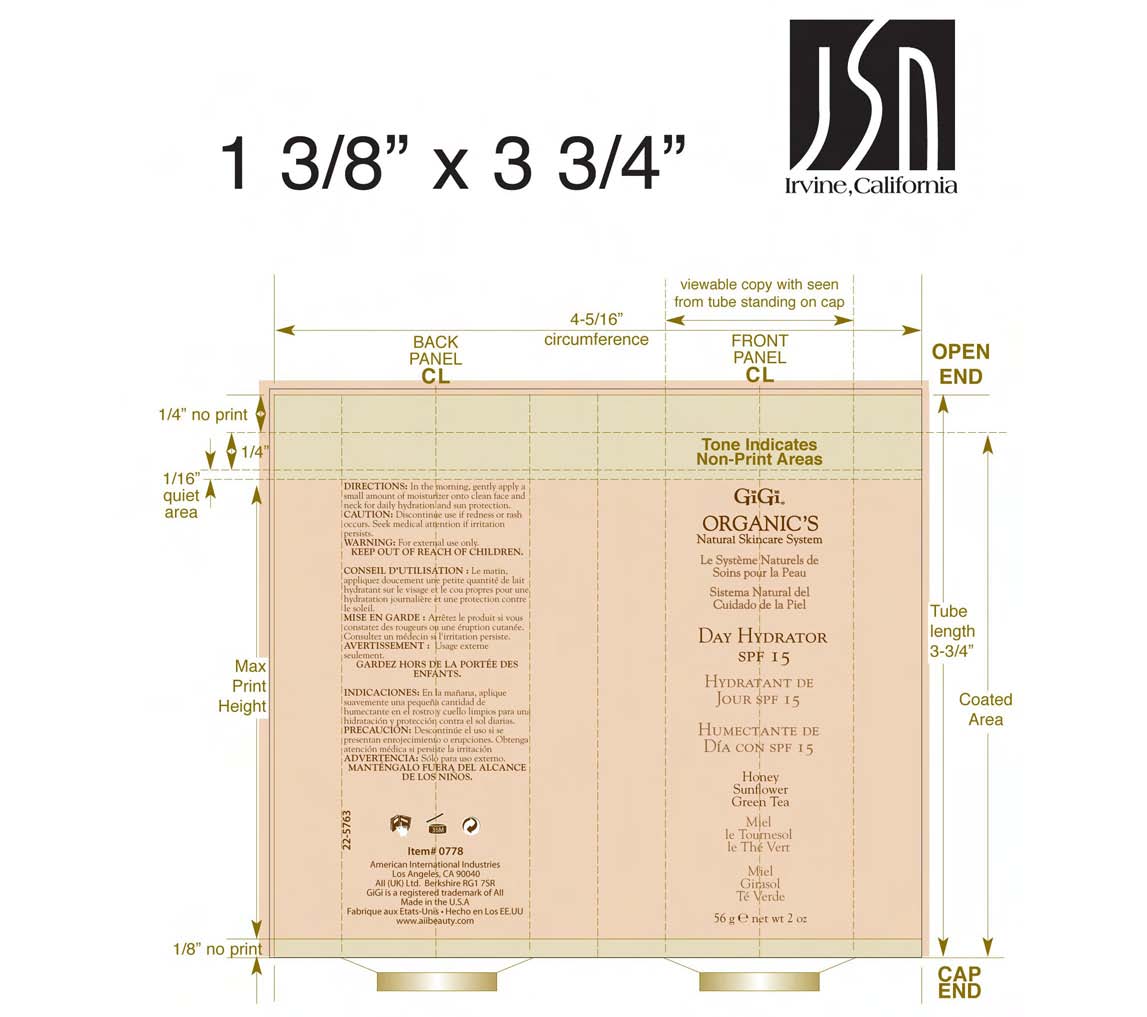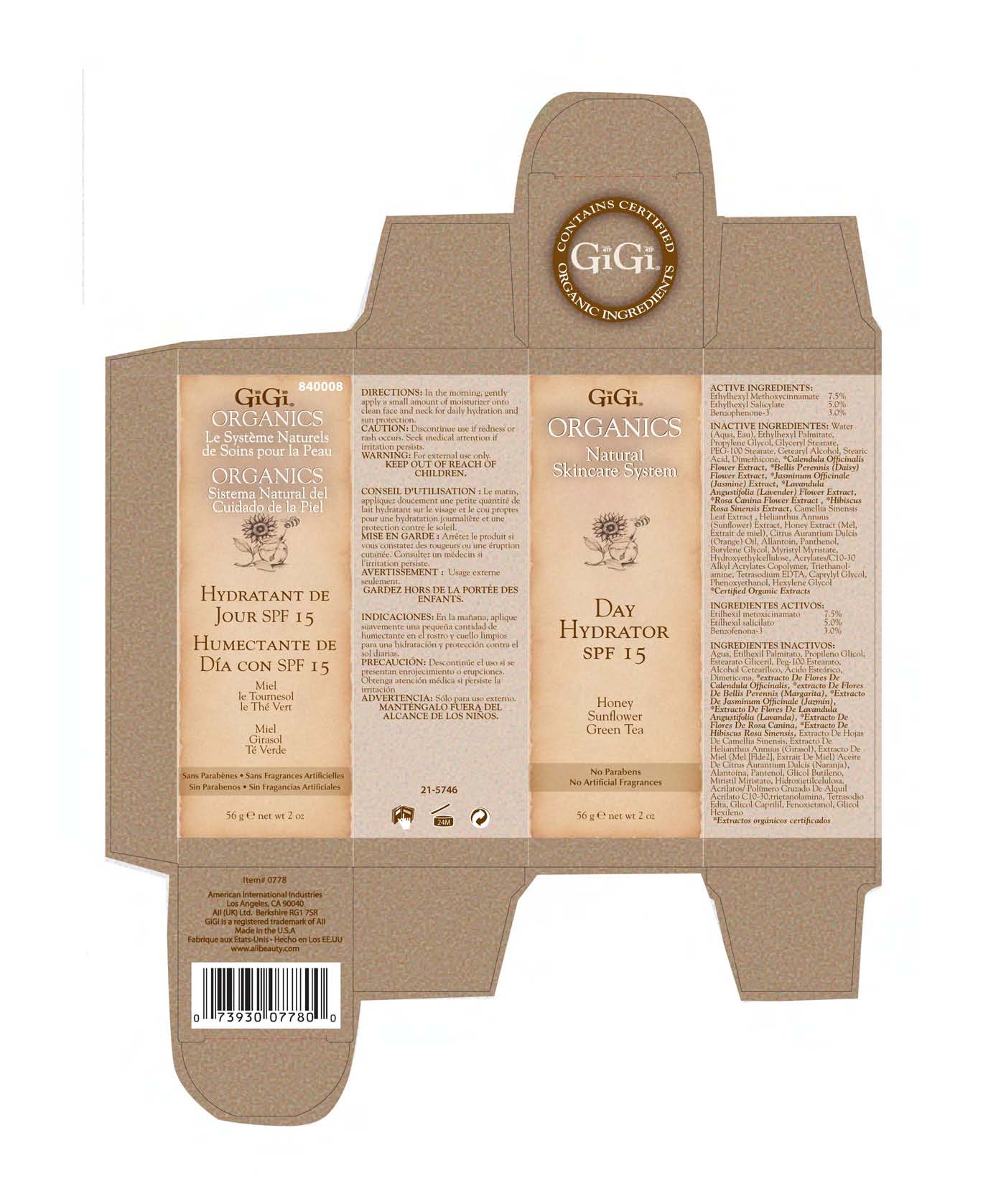 DRUG LABEL: DAY HYDRATOR
NDC: 57367-027 | Form: LOTION
Manufacturer: 220 Laboratories Inc.
Category: otc | Type: HUMAN OTC DRUG LABEL
Date: 20100510

ACTIVE INGREDIENTS: OCTINOXATE 75 mg/1 g; OCTISALATE 50 mg/1 g; OXYBENZONE 30 mg/1 g
INACTIVE INGREDIENTS: WATER; ETHYLHEXYL PALMITATE; PROPYLENE GLYCOL; GLYCERYL MONOSTEARATE; CETOSTEARYL ALCOHOL; POLYOXYL 100 STEARATE; STEARIC ACID; DIMETHICONE; CAPRYLYL GLYCOL; MYRISTYL MYRISTATE; HYDROXYETHYL CELLULOSE (2000 CPS AT 1%); HEXYLENE GLYCOL; TROLAMINE; MYRISTYL LAURATE; ALLANTOIN; EDETATE SODIUM; HELIANTHUS ANNUUS; ORANGE OIL; BUTYLENE GLYCOL; PANTHENOL; HONEY; CALENDULA OFFICINALIS FLOWER; BELLIS PERENNIS; GREEN TEA LEAF; HIBISCUS SABDARIFFA CALYX; JASMINE; LAVENDER; ROSA CANINA FRUIT; PHENOXYETHANOL

DAY HYDRATOR SPF-15 ARTWORK

ACTIVE INGREDIENTS:
Ethylhexyl Methoxycinnamate - 7.5%
Ethylhexyl Salicylate - 5.0%
Benzophenone-3 - 3.0%

DOSAGE AND ADMINISTRATION

DIRECTIONS: In the morning, gently apply a small amount of moisturizer onto clean face and neckfor daily hydration and skin protection.

GENERAL PRECAUTIONS

CAUTION: Discontinue use if redness or rash occurs. Seek medical attention if irritation persists.

WARNINGS

WARNING: For external use only.

KEEP OUT OF REACH OF CHILDREN.

PACKAGE LABEL

GiGi ORGANICS
Natural Skincare System
DAY HYDRATOR
SPF 15
Honey
Sunflower
Green Tea